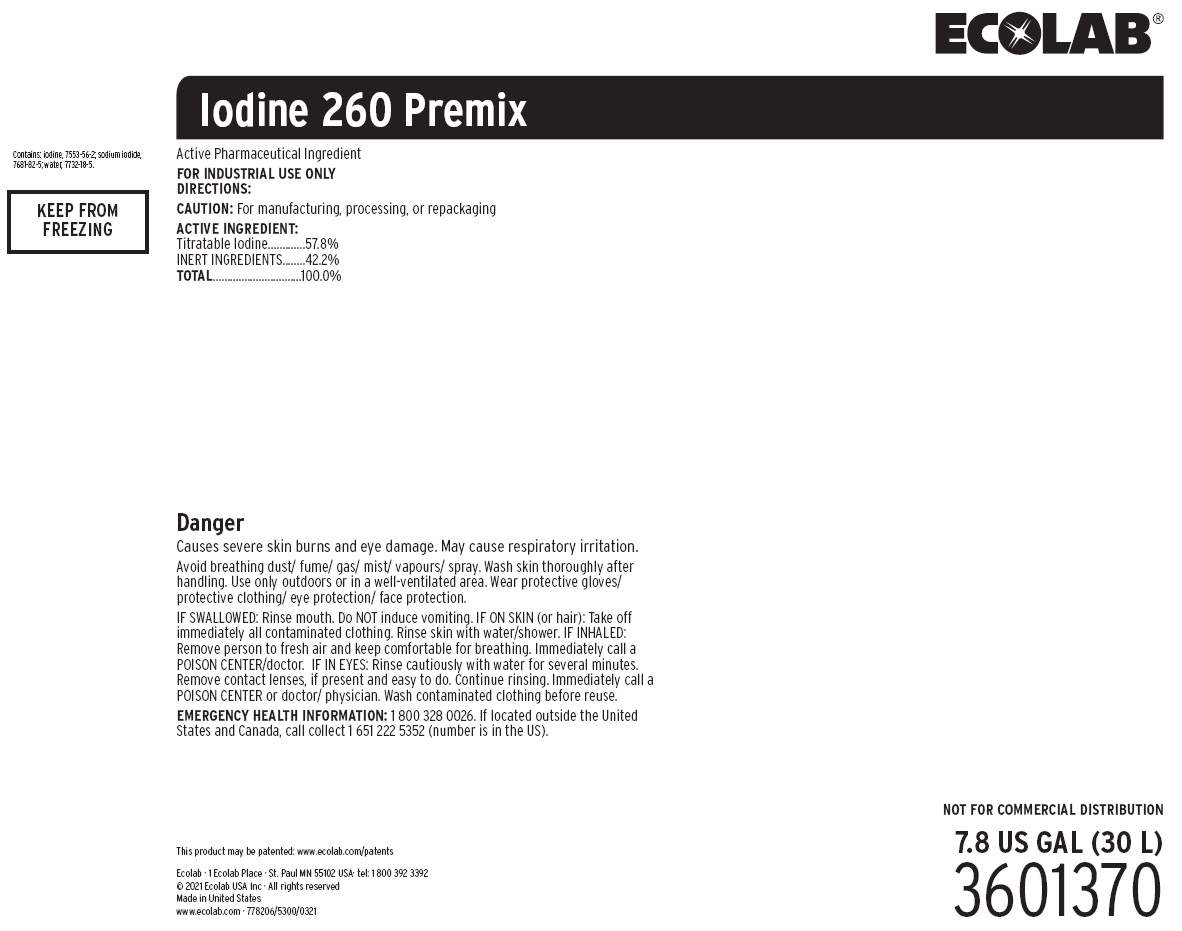 DRUG LABEL: Iodine 260 Premix
NDC: 47593-642 | Form: SOLUTION
Manufacturer: Ecolab Inc.
Category: other | Type: BULK INGREDIENT - ANIMAL DRUG
Date: 20220209

ACTIVE INGREDIENTS: IODINE 578 mg/1 mL
INACTIVE INGREDIENTS: SODIUM HYDROXIDE; WATER; FORMIC ACID

SAFE HANDLING WARNING

Avoid breathing dust/ fume/ gas/ mist/ vapours/ spray. Wash skin thoroughly after handling. Use only outdoors or in a well-ventilated area. Wear protective gloves/ protective clothing/ eye protection/ face protection.

IF SWALLOWED: Rinse mouth. Do NOT induce vomiting. IF ON SKIN (or hair): Take off immediately all contaminated clothing. Rinse skin with water/shower. IF INHALED: Remove person to fresh air and keep comfortable for breathing. Immediately call a POISON CENTER/doctor. IF IN EYES: Rinse cautiously with water for several minutes. Remove contact lenses, if present and easy to do. Continue rinsing. Immediately call a POISON CENTER or doctor/ physician. Wash contaminated clothing before reuse.

VETERINARY INDICATIONS

Active Pharmaceutical Ingredient

FOR INDUSTRIAL USE ONLY

OTHER SAFETY INFORMATION

Danger

Causes severe skin burns and eye damage. May cause respiratory irritation.

EMERGENCY HEALTH INFORMATION: 1 800 328 0026. If located outside the United States and Canada, call collect 1 651 222 5352 (number is in the US).

Principal display panel and representative container

Iodine 260 Premix

Active Pharmaceutical Ingredient

FOR INDUSTRIAL USE ONLY

DIRECTIONS:

CAUTION: For manufacturing, processing, or repackaging

ACTIVE INGREDIENT:

Titratable Iodine.............57.8%

INERT INGREDIENTS........42.2%

TOTAL...............................100.0%

NOT FOR COMMERCIAL DISTRIBUTION

7.8 US GAL (30 L)

3601370

This product may be patented: www.ecolab.com/patents

Ecolab · 1 Ecolab Place · St. Paul MN 55102 USA· tel: 1 800 392 3392

© 2021 Ecolab USA Inc · All rights reserved

Made in United States

www.ecolab.com · 778206/5300/0321